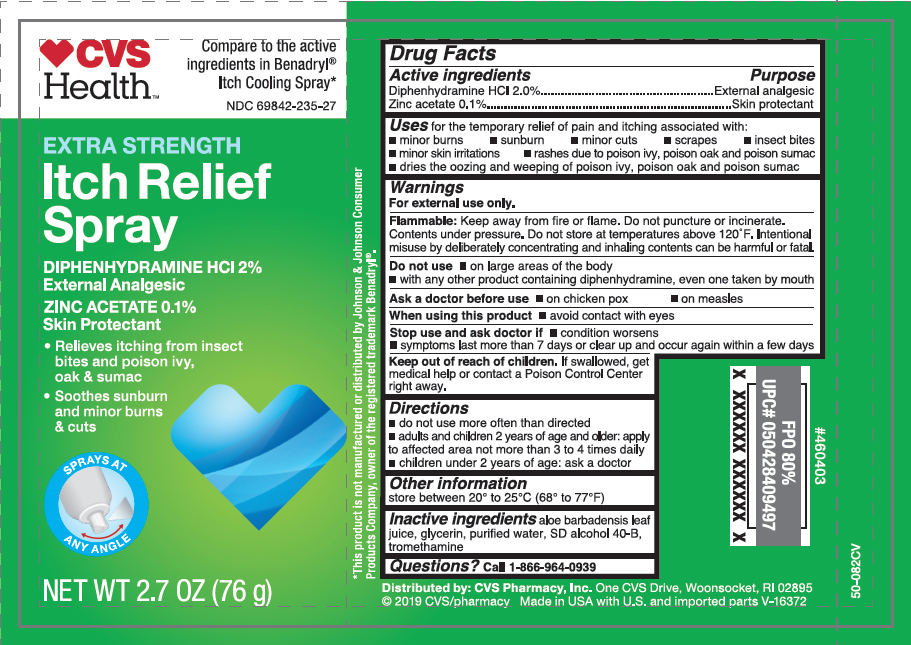 DRUG LABEL: Itch Relief
NDC: 69842-235 | Form: AEROSOL, SPRAY
Manufacturer: CVS Pharmacy
Category: otc | Type: HUMAN OTC DRUG LABEL
Date: 20251029

ACTIVE INGREDIENTS: DIPHENHYDRAMINE HYDROCHLORIDE 1.5 g/76 g; ZINC ACETATE 0.076 g/76 g
INACTIVE INGREDIENTS: GLYCERIN; ALCOHOL; TROMETHAMINE; ALOE VERA LEAF; WATER

CVS Itch Relief Continuous Spray

Active ingredients

Diphenhydramine HCl 2%,
Zinc Acetate 0.1%

Purpose

- External analgesic
- Skin protectant

Uses

for the temporary relief of pain and itching associated with:

- minor burns
- sunburns
- minor cuts
- scrapes
- insect bites
- minor skin irritations
- rashes due to poison ivy, poison oak and poison sumac
- dries the oozing and weeping of poison ivy, poison oak and poison sumac

Warnings

For external use only.

Flammable:

Keep away from fire or flame. Do not puncture or incinerate. Contents under pressure. Do not store at temperatures above 120°F. Intentional misuse by delibrately concenrating and inhaling contents can be harmful or fatal.

Do not use

- on large areas of the body
- with any other product containing diphenhydramine, even one taken by mouth

Stop use and ask doctor if

- conditions worsens
- symptoms last more than 7 days or clear up and occur again within a few days

When using this product

- avoid contact with eyes
- use only as directed

Keep out of reach of children.

If swallowed, get medical help or contact a Poison Control Center right away.

Directions

- adults and children 2 years of age and older: apply to affected area not more than 3 to 4 times daily
- children under 2 years of age: ask a doctor

Other information

store between 20° to 25°C (68° to 77°F)

Inactive ingredients

aloe barbadensis leaf juice, glycerin, purified water, sd alcohol 40-B, tromethamine

Questions?

1-866-964-0939

Principal Display Panel

CVS Health

EXTRA STRENGTH

Itch Relief Spray

DIPENHYDRAMINE HCL 2%

External Analgesic

ZINC ACETATE 0.1%

Skin Protectant

- Relieves itching from insect bites and poison ivy, oak & sumac
- Soothes sunburn and minor burns & cuts

NET WT 2.7 OZ(76g)